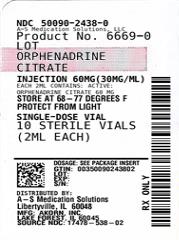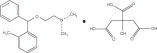 DRUG LABEL: Orphenadrine Citrate
NDC: 50090-2438 | Form: INJECTION
Manufacturer: A-S Medication Solutions
Category: prescription | Type: HUMAN PRESCRIPTION DRUG LABEL
Date: 20210223

ACTIVE INGREDIENTS: ORPHENADRINE CITRATE 30 mg/1 mL
INACTIVE INGREDIENTS: Sodium Chloride 5.8 mg/1 mL; Sodium Metabisulfite 2.0 mg/1 mL; Sodium Hydroxide; Water

ORPHENADRINE CITRATE INJECTION, USP

Rx only

DESCRIPTION:

Orphenadrine citrate is the citrate salt of orphenadrine ((±)-N, N-Dimethyl- 2-[(o-methyl-a-phenylbenzyl)oxy]ethylamine citrate (1:1)) with a molecular weight of 461.50; empirical formula C18H23NO•C6H8O7. The structural formula of orphenadrine citrate is:

It occurs as a white, crystalline powder having a bitter taste. It is practically odorless; sparingly soluble in water, slightly soluble in alcohol.

Orphenadrine citrate injection contains 60 mg of orphenadrine citrate in aqueous solution in each vial. Orphenadrine citrate injection also contains: sodium chloride USP 5.8 mg; sodium metabisulfite NF, 2.0 mg; sodium hydroxide NF, to adjust pH (5.0 to 6.0); and water for injection USP, q.s. to 2 mL.

CLINICAL PHARMACOLOGY:

The mode of therapeutic action has not been clearly identified, but may be related to its analgesic properties. Orphenadrine citrate does not directly relax tense muscles in man. Orphenadrine citrate also possesses anti-cholinergic actions.

INDICATIONS AND USAGE:

Orphenadrine citrate injection is indicated as an adjunct to rest, physical therapy, and other measures for the relief of discomfort associated with acute painful musculoskeletal conditions. The mode of action of the drug has not been clearly identified, but may be related to its analgesic properties. Orphenadrine citrate does not directly relax tense skeletal muscles in man.

CONTRAINDICATIONS:

Contraindicated in patients with glaucoma, pyloric or duodenal obstruction, stenosing peptic ulcers, prostatic hypertrophy or obstruction of the bladder neck, cardio-spasm (megaesophagus) and myasthenia gravis.

Contraindicated in patients who have demonstrated a previous hypersensitivity to the drug.

WARNINGS:

Some patients may experience transient episodes of light-headedness, dizziness or syncope. Orphenadrine citrate may impair the ability of the patient to engage in potentially hazardous activities such as operating machinery or driving a motor vehicle; ambulatory patients should therefore be cautioned accordingly.

Orphenadrine citrate injection contains sodium metabisulfite, a sulfite that may cause allergic-type reactions including anaphylactic symptoms and life-threatening or less severe asthmatic episodes in certain susceptible people. The overall prevalence of sulfite sensitivity in the general population is unknown and probably low. Sulfite sensitivity is seen more frequently in asthmatic than nonasthmatic people.

PRECAUTIONS:

Confusion, anxiety and tremors have been reported in few patients receiving propoxyphene and orphenadrine concomitantly. As these symptoms may be simply due to an additive effect, reduction of dosage and/or discontinuation of one or both agents is recommended in such cases.

Orphenadrine citrate should be used with caution in patients with tachycardia, cardiac decompensation, coronary insufficiency, cardiac arrhythmias.

Safety of continuous long-term therapy with orphenadrine has not been established. Therefore, if orphenadrine is prescribed for prolonged use, periodic monitoring of blood, urine and liver function values is recommended.

Pregnancy: Teratogenic Effects: Pregnancy Category C.

Safe use of orphenadrine has not been established with respect to adverse effects upon fetal development. Therefore, orphenadrine should be used in women of childbearing potential and particularly during early pregnancy only when in the judgment of the physician the potential benefits outweigh the possible hazards.

Pediatric Use:

Safety and effectiveness in children have not been established; therefore, this drug is not recommended for use in the pediatric age group.

ADVERSE REACTIONS:

Adverse reactions of orphenadrine are mainly due to the mild anti- cholinergic action of orphenadrine, and are usually associated with higher dosage. Dryness of the mouth is usually the first adverse effect to appear. When the daily dose is increased, possible adverse effects include: tachycardia, palpitation, urinary hesitancy or retention, blurred vision, dilatation of pupils, increased ocular tension, weakness, nausea, vomiting, headache, dizziness, constipation, drowsiness, hypersensitivity reactions, pruritus, hallucinations, agitation, tremor, gastric irritation, and rarely urticaria and other dermatoses. Infrequently, an elderly patient may experience some degree of mental confusion. These adverse reactions can usually be eliminated by reduction in dosage. Very rare cases of aplastic anemia associated with the use of orphenadrine tablets have been reported. No causal relationship has been established.

Rare instances of anaphylactic reaction have been reported associated with the intramuscular injection of orphenadrine citrate injection.

DRUG ABUSE AND DEPENDENCE:

Orphenadrine has been chronically abused for its euphoric effects. The mood elevating effects may occur at therapeutic doses of orphenadrine.

OVERDOSAGE:

Orphenadrine is toxic when overdosed and typically induces anticholinergic effects. In a review of orphenadrine toxicity, the minimum lethal dose was found to be 2 to 3 grams for adults; however, the range of toxicity is variable and unpredictable. Treatment for orphenadrine overdose is evacuation of stomach contents (when necessary), charcoal at repeated doses, intensive monitoring, and appropriate supportive treatment of any emergent anticholinergic effects.

DOSAGE AND ADMINISTRATION:

INJECTION: Adults - One 2 mL vial (60 mg) intravenously or intramuscularly; may be repeated every 12 hours.

HOW SUPPLIED:

Product: 50090-2438

NDC: 50090-2438-0 2 mL in a VIAL / 10 in a CARTON